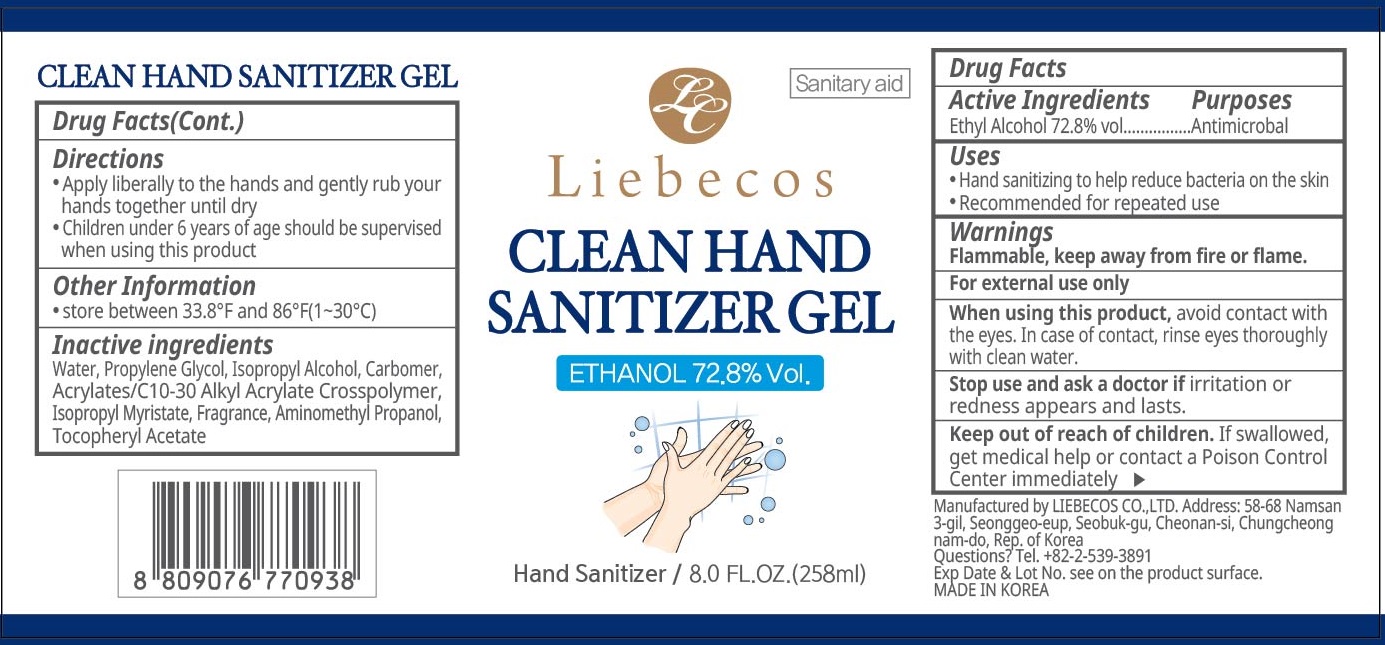 DRUG LABEL: Liebecos Clean Hand Sanitizer
NDC: 75002-010 | Form: GEL
Manufacturer: LIEBECOS CO.,LTD
Category: otc | Type: HUMAN OTC DRUG LABEL
Date: 20200511

ACTIVE INGREDIENTS: Alcohol 72.8 mL/100 mL
INACTIVE INGREDIENTS: Water; Propylene Glycol; Isopropyl Alcohol; CARBOMER HOMOPOLYMER, UNSPECIFIED TYPE; CARBOMER INTERPOLYMER TYPE A (ALLYL SUCROSE CROSSLINKED); Isopropyl Myristate; AMINOMETHYLPROPANOL; .ALPHA.-TOCOPHEROL ACETATE

ACTIVE INGREDIENT

Active ingredients: Ethyl Alcohol 72.8% vol

PURPOSE

Purpose: Antimicrobal

WARNINGS

Flammable, keep away from ﬁre or ﬂame.
For external use only
When using this product, avoid contact with the eyes. In case of contact, rinse eyes thoroughly with clean water.
Stop use and ask a doctor if irritation or redness appears and lasts.

KEEP OUT OF REACH OF CHILDREN

If swallowed, get medical help or contact a Poison Control Center immediately.

Uses

Hand sanitizing to help reduce bacteria on the skin
Recommended for repeated use

Directions

Apply liberally to the hands and gently rub your hands together until dry
Children under 6 years of age should be supervised when using this product

Other information

store between 33.8°F and 86°F(1~30°C)

INACTIVE INGREDIENT

Inactive ingredients:

Water, Propylene Glycol, Isopropyl Alcohol, Carbomer, Acrylates/C10-30 Alkyl Acrylate Crosspolymer, Isopropyl Myristate, Fragrance, Aminomethyl Propanol, Tocopheryl Acetate